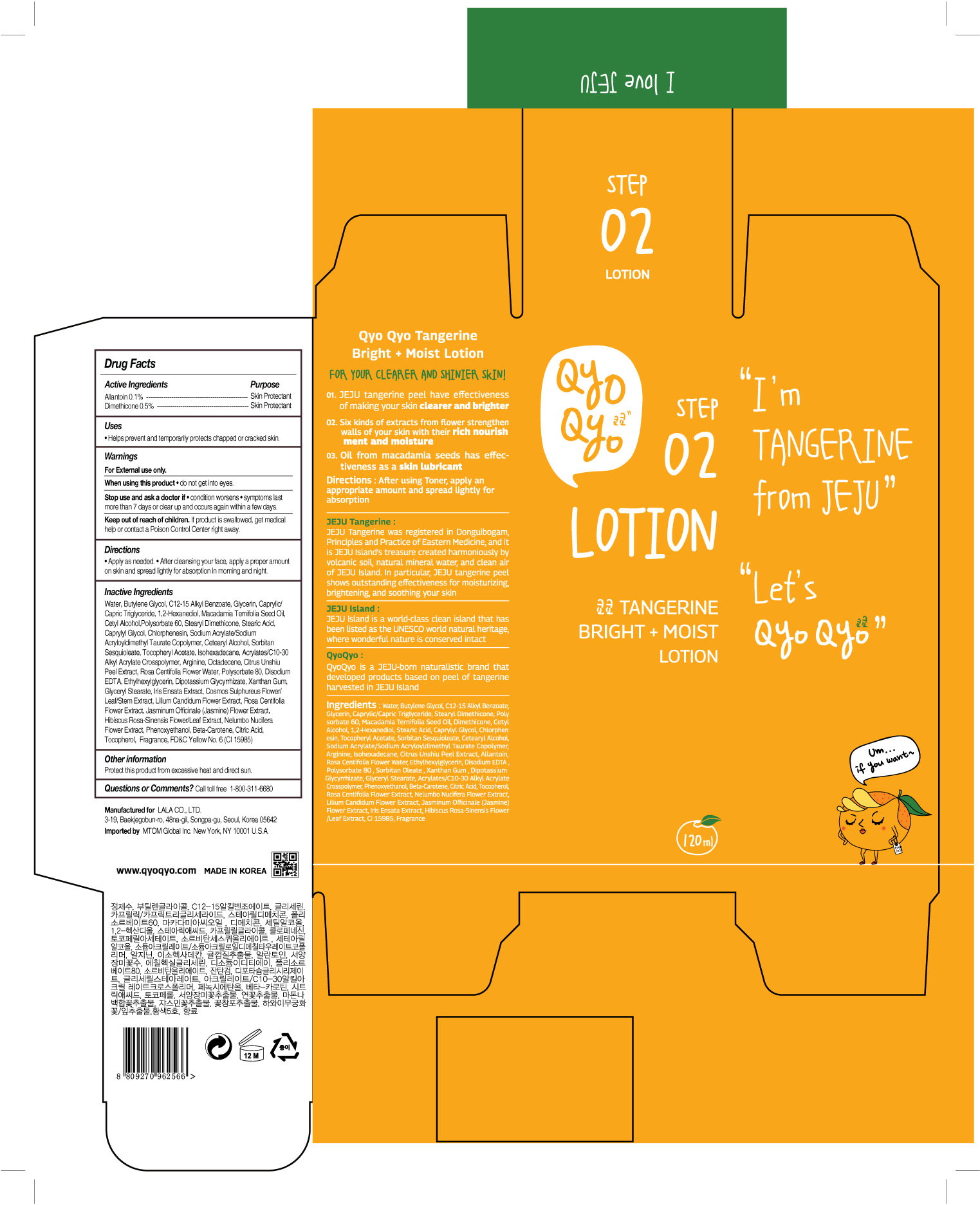 DRUG LABEL: QYO QYO Tangerine Bright Moist
NDC: 71733-103 | Form: LOTION
Manufacturer: LaLa Co., Ltd.
Category: otc | Type: HUMAN OTC DRUG LABEL
Date: 20190101

ACTIVE INGREDIENTS: DIMETHICONE 0.5 g/120 mL; ALLANTOIN 0.1 g/120 mL
INACTIVE INGREDIENTS: BUTYLENE GLYCOL; TANGERINE PEEL; WATER; GLYCERIN

Qyo Qyo Tangerine Bright + Moist Lotion

ACTIVE INGREDIENTS

ALLANTOIN 0.1%

DIMETHICONE 0.5%

PURPOSE

SKIN PROTECTANT

USES

- Helps prevent and temporarily protects chapped or cracked skin.

WARNINGS

For external use only.

When using this product • do not get into eyes.

STOP USE

Stop us and ask doctor if • condition worsens • symptoms last
more than 7 days or clear up and occurs again within a few days.

Keep out of reach of children. If product is swallowed, get medical help or contact a Poison Control Center right away.

Directions

• Apply as needed. • After cleansing your face, apply a proper amount on skin and spread lightly for absorption.

Inactive Ingredients

Water, Butylene Glycol, C12-15 Alkyl Benzoate, Glycerin, Caprylic/ Capric Triglyceride, 1,2-Hexanediol, Macadamia Ternifolia Seed Oil, Cetyl Alcohol,Polysorbate 60, Stearyl Dimethicone, Stearic Acid, Caprylyl Glycol, Chlorphenesin, Sodium Acrylate/Sodium Acryloyldimethyl Taurate Copolymer, Cetearyl Alcohol, Sorbitan Sesquioleate, Tocopheryl Acetate, Isohexadecane, Acrylates/C10-30 Alkyl Acrylate Crosspolymer, Arginine, Octadecene, Citrus Unshiu Peel Extract, Rosa Centifolia Flower Water, Polysorbate 80, Disodium EDTA, Ethylhexylglycerin, Dipotassium Glycyrrhizate, Xanthan Gum, Glyceryl Stearate, Iris Ensata Extract, Cosmos Sulphureus Flower/ Leaf/Stem Extract, Lilium Candidum Flower Extract, Rosa Centifolia Flower Extract, Jasminum Officinale (Jasmine) Flower Extract, Hibiscus Rosa-Sinensis Flower/Leaf Extract, Nelumbo Nucifera Flower Extract, Phenoxyethanol, Beta-Carotene, Citric Acid, Tocopherol, Fragrance, FD&C Yellow No. 6 (CI 15985)

Other Information

Protect this product from excessive heat and direct sun.

Questions or Comments?

Call toll free 1-800-311-6680